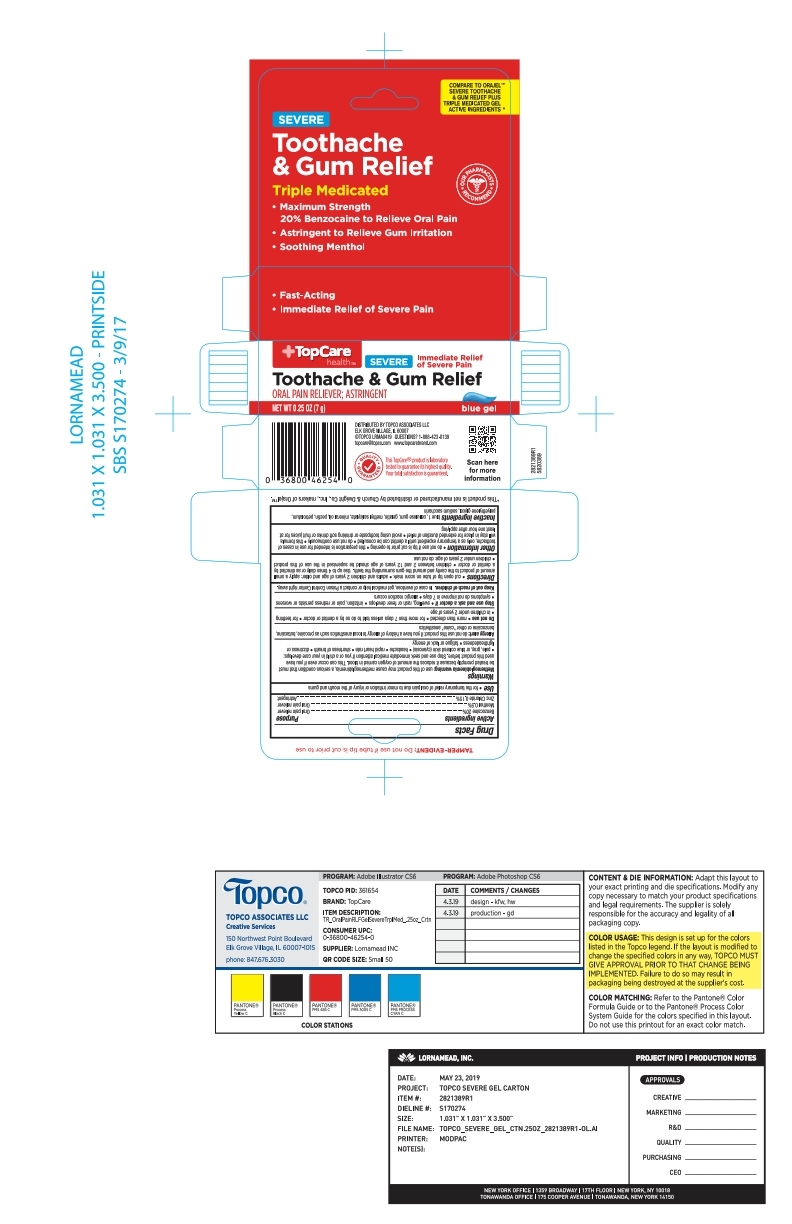 DRUG LABEL: Severe Triple Medicated Gel
NDC: 36800-389 | Form: GEL
Manufacturer: Topco
Category: otc | Type: HUMAN OTC DRUG LABEL
Date: 20201116

ACTIVE INGREDIENTS: MENTHOL, UNSPECIFIED FORM 0.55 g/100 g; ZINC CHLORIDE 0.15 g/100 g; BENZOCAINE 20 g/100 g
INACTIVE INGREDIENTS: PETROLATUM; MINERAL OIL; GELATIN, UNSPECIFIED; POLYETHYLENE GLYCOL 1000; FD&C BLUE NO. 1; PECTIN; CARBOXYMETHYLCELLULOSE SODIUM, UNSPECIFIED FORM; METHYL SALICYLATE; SACCHARIN SODIUM

TopCare 3x Medicated OP Gel

ACTIVE INGREDIENT

Benzocaine 20%

Menthol 0.5%

Zinc Chloride 0.15%

PURPOSE

Oral pain reliever

Oral pain reliever

Astringent

INDICATIONS AND USAGE

for the temporary relief of oral pain due to minor irritation or injury of the mouth and gums

WARNINGS

Methemoglobinemia warning: use of this product may cause methemoglobinemia, a serious condition that must be treated promptly because it reduces the amount of oxygen carried in blood. This can occur even if you have used this product before. Stop use and seek immediate medical attention if you or a child in your care develops: pale, gray, or blue colored skin (cyanosis) * headache * rapid heart rate * shortness of breath * dizziness or lightheadedness * fatigue or lack of energy

Allergy alert: do not use this product if you have a history of allergy to local anesthetics such as procaine, butacaine, benzocaine or other "caine" anesthetics

Do not use * more that directed * for more than 7 days unless told to do so by a dentist or doctor * for teething * in children under 2 years of age

Stop use and ask a doctor if * swelling, rash or fever develops * irritation, pain or redness persists or worsens * symptoms do not improve in 7 days * allergice reaction occurs

Keep out of reach of children. In case of overdose, get medical help or contact a Poison Control Center right away.

DOSAGE AND ADMINISTRATION

cut open tip of tube on score mark * adults and children 2 years of age and older: apply a small amount of product to the cavity and around the gum surrounding the teeth. Use up to 4 times daily or as directed by a dentist or doctor * children between 2 and 12 years of age should be supervised in the use of this product * children under 2 years of age: do not use

do not use if tip is cut prior to opening * this preparation is intended for use in cases of toothache, only as a temporary expedient until a dentist can be consulted * do not use continuously * this formula will stay in place for extended duration of relief * avoid using toothpaste or drinking soft drinks or fruit juices for at least one hour after applying

INACTIVE INGREDIENT

blue 1, cellulose gum, gelatin, methyl salicylate, mineral oil, pectin, petrolatum, polyethylene glycol, sodium saccharin